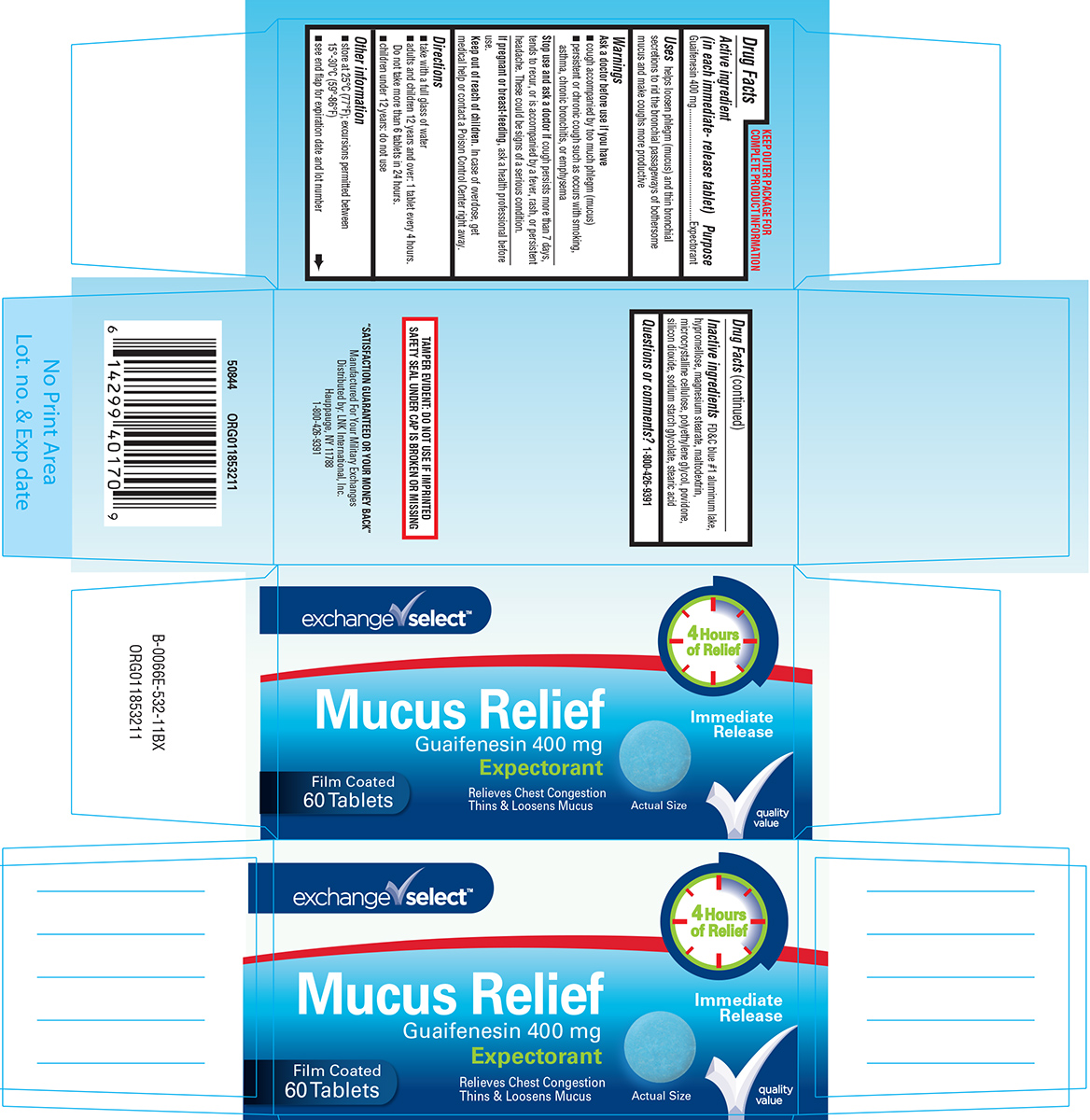 DRUG LABEL: Mucus Relief
NDC: 55301-932 | Form: TABLET, FILM COATED
Manufacturer: ARMY AND AIR FORCE EXCHANGE SERVICE
Category: otc | Type: HUMAN OTC DRUG LABEL
Date: 20240827

ACTIVE INGREDIENTS: GUAIFENESIN 400 mg/1 1
INACTIVE INGREDIENTS: FD&C BLUE NO. 1 ALUMINUM LAKE; HYPROMELLOSE, UNSPECIFIED; MAGNESIUM STEARATE; MALTODEXTRIN; MICROCRYSTALLINE CELLULOSE; POLYETHYLENE GLYCOL, UNSPECIFIED; POVIDONE, UNSPECIFIED; SILICON DIOXIDE; SODIUM STARCH GLYCOLATE TYPE A POTATO; STEARIC ACID

Exchange Select 44-532 Delisted

Active ingredient (in each immediate-release tablet)

Guaifenesin 400 mg

Purpose

Expectorant

Uses

helps loosen phlegm (mucus) and thin bronchial secretions to rid the bronchial passageways of bothersome mucus and make coughs more productive

Warnings

Ask a doctor before use if you have

- cough accompanied by too much phlegm (mucus)
- persistent or chronic cough such as occurs with smoking, asthma, chronic bronchitis, or emphysema

Stop use and ask a doctor if

cough persists more than 7 days, tends to recur, or is accompanied by a fever, rash, or persistent headache. These could be signs of a serious condition.

If pregnant or breast-feeding,

ask a health professional before use.

Keep out of reach of children.

In case of overdose, get medical help or contact a Poison Control Center right away.

Directions

- take with a full glass of water
- adults and children 12 years and over: 1 tablet every 4 hours. Do not take more than 6 tablets in 24 hours.
- children under 12 years: do not use

Other information

- store at 25°C (77°F); excursions permitted between 15°-30°C (59°-86°F)
- see end flap for expiration date and lot number

Inactive ingredients

FD&C blue #1 aluminum lake, hypromellose, magnesium stearate, maltodextrin, microcrystalline cellulose, polyethylene glycol, povidone, silicon dioxide, sodium starch glycolate, stearic acid

Questions or comments?

1-800-426-9391

Principal Display Panel

exchange✓select™

Mucus Relief
Guaifenesin 400 mg
Expectorant

Relieves Chest Congestion
Thins & Loosens Mucus

4 Hours
of Relief

Immediate
Release

Film Coated
60 Tablets

Actual Size

✓quality
value

TAMPER EVIDENT: DO NOT USE IF IMPRINTED
SAFETY SEAL UNDER CAP IS BROKEN OR MISSING

"SATISFACTION GUARANTEED OR YOUR MONEY BACK"
Manufactured For Your Military Exchanges
Distributed by: LNK International, Inc.
Hauppauge, NY 11788
1-800-426-9391

50844 ORG011853211

Exchange Select 44-532